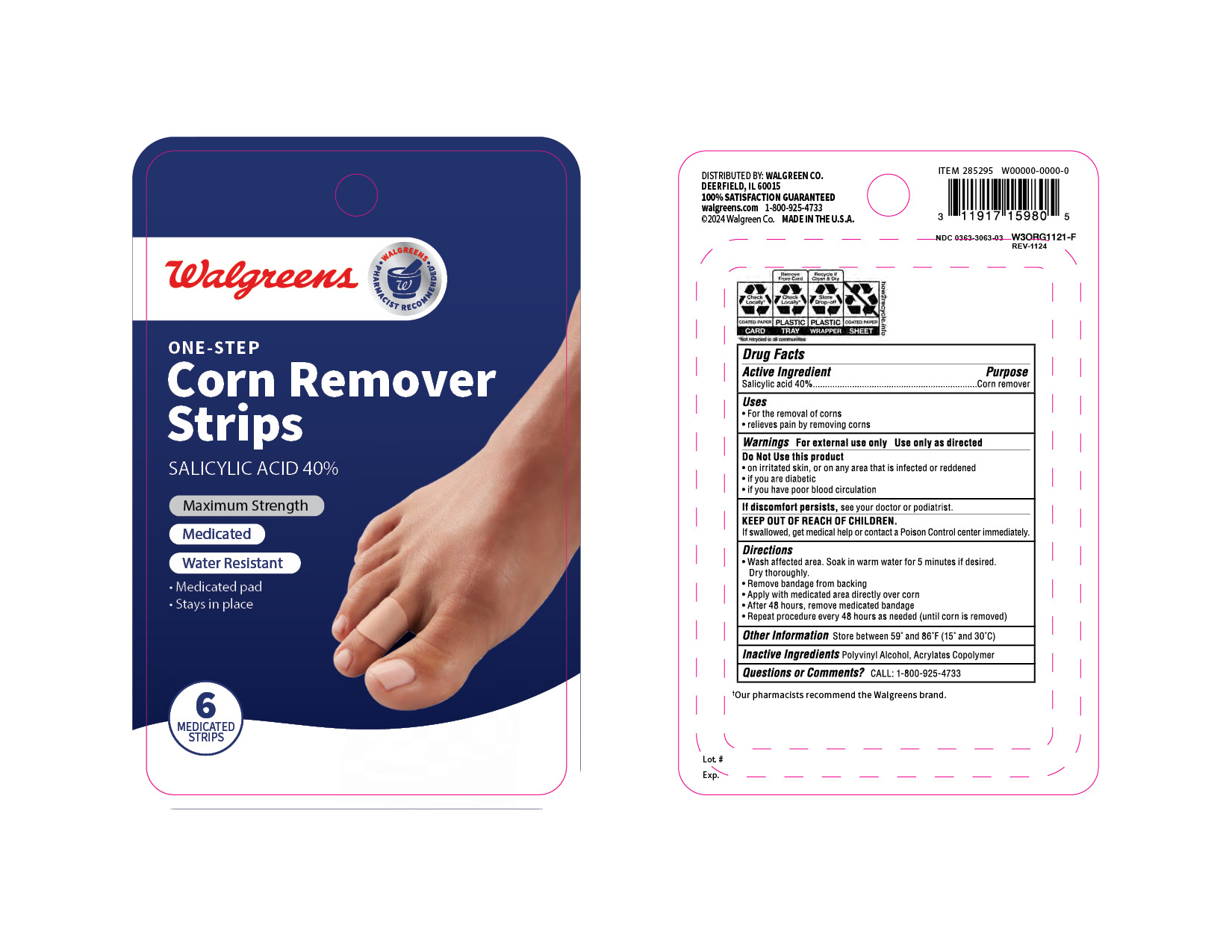 DRUG LABEL: Walgreens Corn Remover
NDC: 0363-3063 | Form: STRIP
Manufacturer: WALGREENS Co
Category: otc | Type: HUMAN OTC DRUG LABEL
Date: 20250502

ACTIVE INGREDIENTS: SALICYLIC ACID 4.42 mg/1 1
INACTIVE INGREDIENTS: POLYVINYL ALCOHOL; HIGH DENSITY POLYETHYLENE; VINYL ACETATE

Walgreens Corn Remover Strips

Drug Facts

Active Ingredient

Salicylic acid 40%

Purpose

Corn remover

Uses

- For the removal of corns
- relieves pain by removing corns

Warnings

For external use only
Use only as directed

Do Not Use

- if you are diabetic
- on irritated, broken or infected skin
- if you have poor blood circulation

If discomfort persists, see your doctor or podiatrist.

KEEP OUT OF REACH OF CHILDREN.

If swallowed, get medical help or contact a Poison Control center immediately.

Directions

- Wash affected area. Soak in warm water for 5 minutes if desired. Dry thoroughly.
- Remove bandage from backing
- Apply with medicated area directly over corn
- After 48 hours, remove medicated bandage
- Repeat procedure every 48 hours as needed (until corn is removed) for up to 14 days

Other Information

Store between 59° and 86°F (15° and 30°C)

Inactive Ingredients

Polyvinyl Alcohol, Acrylic Copolymer

Questions or Comments?

CALL: 1-800-925-4733

DISTRIBUTED BY: WALGREEN CO.
200 WILMOT RD., DEERFIELD, IL 60015

PRINCIPAL DISPLAY PANEL - 6 Strip Box

Well at
Walgreens

WALGREENS PHARMACIST RECOMMENDED‡

NEW

MAXIMUM STRENGTH • ONE-STEP

Corn Remover
Strips

Salicylic Acid 40%

- Removes corns in as
  few as two treatments*
- Water resistant
- Medicated pad
- Stays in place

MEDICATED
STRIPS

Compare to Dr. Scholl's® OneStep
Corn Removers active ingredient‡‡